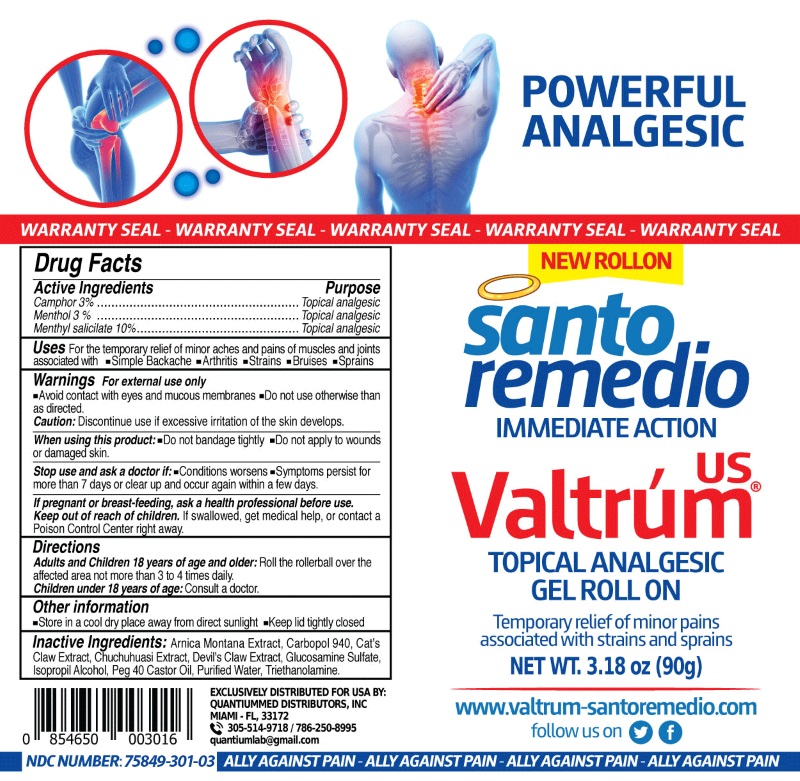 DRUG LABEL: Valtrum Topical Analgesic Roll On
NDC: 75849-301 | Form: GEL
Manufacturer: LABORATORIOS QUANTIUM LLC
Category: otc | Type: HUMAN OTC DRUG LABEL
Date: 20231109

ACTIVE INGREDIENTS: METHYL SALICYLATE 10 g/100 g; MENTHOL, UNSPECIFIED FORM 3 g/100 g; CAMPHOR (NATURAL) 3 g/100 g
INACTIVE INGREDIENTS: ARNICA MONTANA WHOLE; CARBOMER HOMOPOLYMER TYPE C (ALLYL PENTAERYTHRITOL CROSSLINKED); CAT'S CLAW; MAYTENUS MACROCARPA BARK; HARPAGOPHYTUM PROCUMBENS ROOT; GLUCOSAMINE SULFATE; ISOPROPYL ALCOHOL; PEG-40 SORBITAN DIISOSTEARATE; TROLAMINE; WATER

ACTIVE INGREDIENTS

Active Ingredients | Purpose
Methyl Salicylate 10% | Topical Analgesic
Menthol 3% | Topical Analgesic
Camphor 3% | Topical Analgesic

INACTIVE INGREDIENT

Arnica Montana Extract, Carbopol 940,Cat's Claw Extract, Chuchuhuasi Extract, Devil's Claw Extract, Glucosamine Sulfate,Isopropil Alcohol, Peg 40 Castor Oil, Purified Water, Triethanolamine

WARNINGS

For the external use only.

- Avoid contact with eyes and mucous membranes.
- Do not use otherwise than as directed

Caution:Discontinue use if excessive irritation of the skin develops.

When using this product use as directed.

- Do not bandage tightly.
- Do not apply to wounds or damaged skin.

Stop use and ask a doctor if:

- Conditions worsens
- Symptoms persist for more than 7 days or clear up and occur again within a few days

If pregnant or breast-feeding

Ask a health professional before use.

DOSAGE & ADMINISTRATION

Adults and children 18 years of age and older: Spray a thin layer over the affected area not more than 3 to 4 times daily.
Children under 18 years of age: Consult a doctor.

PURPOSE

For temporary relief of minor aches and pains of muscles and joints associated with simple backache, arthritis, strains, bruises, sprains.

Santo Remedio Aerobic Sports

QUANTIUMMED DISTRIBUTORS, INC
MIAMI - FL, 33172